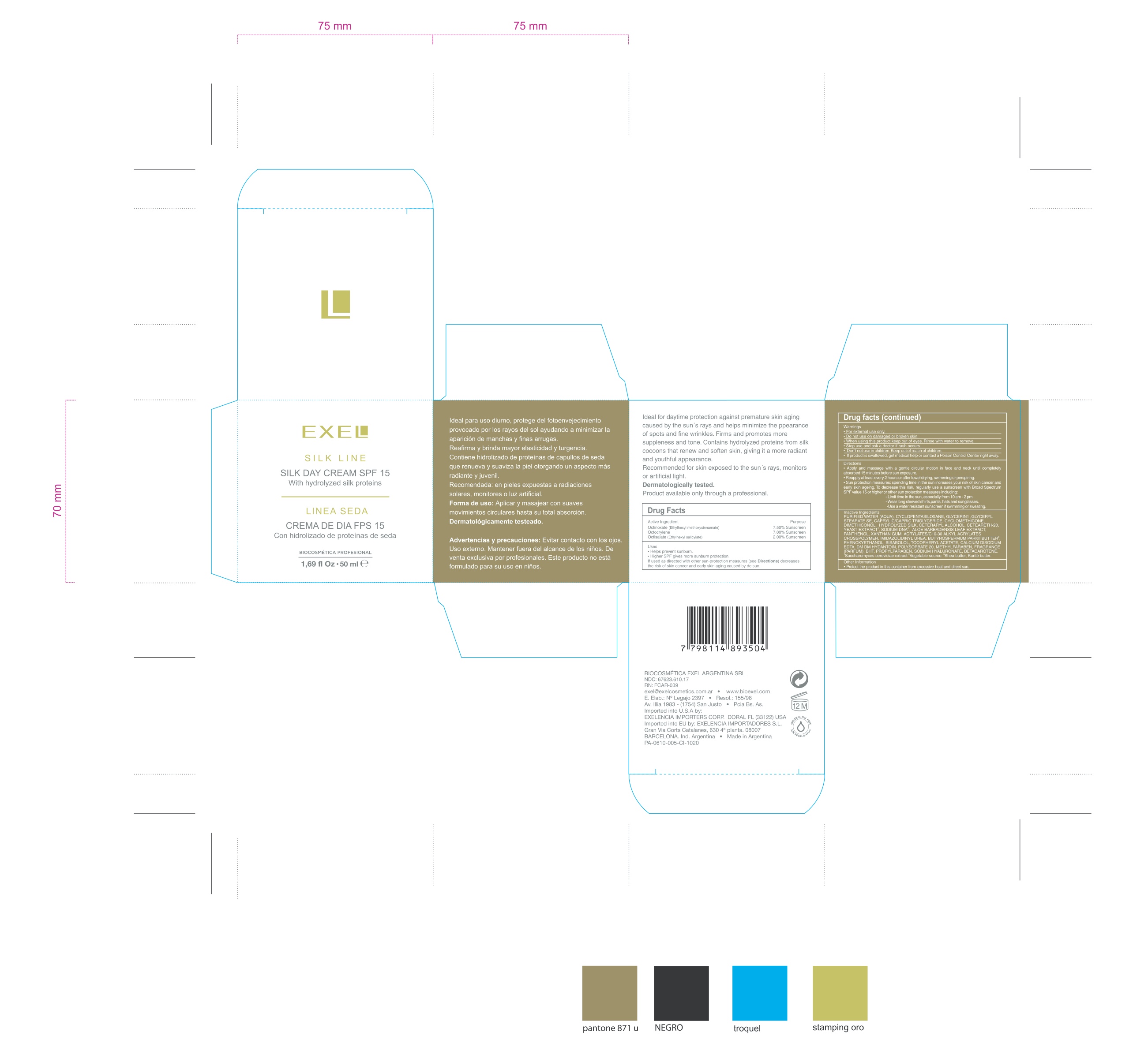 DRUG LABEL: Silk Line Silk Day Cream SPF 15
NDC: 53863-003 | Form: CREAM
Manufacturer: Exelencia Importers, Corp.
Category: otc | Type: HUMAN OTC DRUG LABEL
Date: 20240630

ACTIVE INGREDIENTS: OCTOCRYLENE 7 g/100 mL; OCTISALATE 2 g/100 mL; OCTINOXATE 7.5 g/100 mL
INACTIVE INGREDIENTS: CARBOMER INTERPOLYMER TYPE A (ALLYL SUCROSE CROSSLINKED); SHEA BUTTER; PHENOXYETHANOL; CYCLOMETHICONE 5; WATER; LEVOMENOL; PROPYLPARABEN; BETA CAROTENE; HYALURONATE SODIUM; ALOE VERA LEAF; PANTHENOL; BUTYLATED HYDROXYTOLUENE; XANTHAN GUM; MEDIUM-CHAIN TRIGLYCERIDES; DIMETHICONOL (40 CST); GLYCERIN; GLYCERYL STEARATE SE; CYCLOMETHICONE; METHYLPARABEN; POLYOXYL 20 CETOSTEARYL ETHER; CETOSTEARYL ALCOHOL; IMIDUREA; DMDM HYDANTOIN; YEAST, UNSPECIFIED; .ALPHA.-TOCOPHEROL ACETATE; EDETATE CALCIUM DISODIUM ANHYDROUS

Silk Line Silk Day Cream SPF 15

Active Ingredient Purpose

Octinoxate(Ethylhexyl methoxycinnamate) 7.5% Sunscreen

Octocrylene 7.0% Sunscreen

Octisalate (Ethylhexyl salicylate) 2.0 Sunscreen

Uses

Helps prevent sunburn

Higher SPF gives more sunburn protection

If used as directed with other sun-protection measures (see Directions) decreases the risk of skin cancer and early skin aging caused by de sun

Do not use in children. Keep out of reach of children.

Stop use and ask a doctor if rash occurs

WARNINGS

For external use only.

Do not use on damaged or broken skin.

When using this product keep out of eyes. Rinse with water to remove.

If product is swallowed, get medical help or contact a Poison Control Center right away.

Directions

Apply and massage with a gentle circular motion in face and neck until completely absorbed 15 minutes before sun exposure.
Reapply at least every 2 hours after towel drying, swimming or perspiring.
Sun protection measures: spending time in the sun increases your risk of skin cancer and early skin ageing. To decrease this risk, regularly use a sunscreen with Broad Spectrum SPF value of 15 or higher or other sun protection measures including:
Limit time in the sun, especially between 10am-2pm
Wear long sleeved shirts, pants, hats and sunglasses
Use a water resistant sunscreen if swimming or sweating.

Inactive ingredients

Purified Water (aqua), Cyclopentasiloxane, Glycerin1, Glyceryl Stearate SE, Caprylic/Capric Triglyceride, Cyclomethicone, Dimethiconol, Hydrolyzed Silk, Ceteraryl Alcohol, Ceteareth-20, Yeast Extract, Sodium DNA, Aloe Barbadensis Leaf Extract, Panthenol, Xanthan Gum, Acrylates/C10-30 Alkyl Acrylates Crosspolymer, Imidazolinyl Urea, Butyrospermum Parkii Butter, Phenoxyethanol, Bisabolol, Tocopheryl Acetate, Calcium Disodium EDTA, DM DM Hydantoin, Polysorbate 20, Methylparaben, Fragrance (parfum), BHT, Propylparaben, Sodium Hyaluronate, Betacarotene

PACKAGE LABEL

Exel

Silk Line

Silk Day Cream SPF 15

with hydrolyzed silk proteins

Linea Seda

Crema De Dia FPS 15

Con hydrolizado de proteinas de seda

Biocosmetica Proffesional

1,69 fl Oz 50 ml